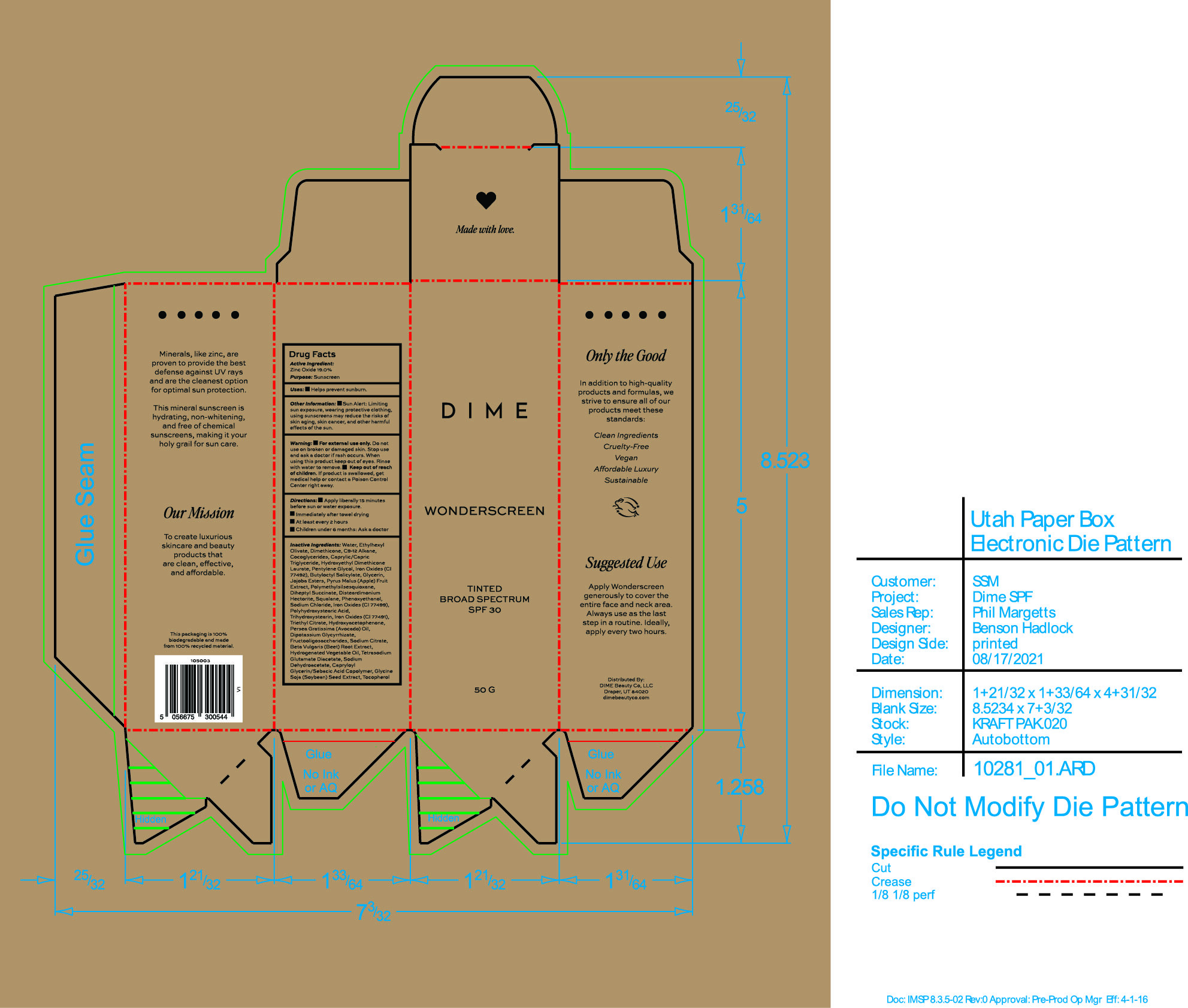 DRUG LABEL: Wonderscreen Tinted Broad Spectrum SPF 30 Shade 3
NDC: 82870-008 | Form: CREAM
Manufacturer: Dime Beauty Co, LLC
Category: otc | Type: HUMAN OTC DRUG LABEL
Date: 20251001

ACTIVE INGREDIENTS: ZINC OXIDE 19 g/100 g
INACTIVE INGREDIENTS: PENTYLENE GLYCOL; TETRASODIUM GLUTAMATE DIACETATE; COCO-GLYCERIDES; CAPRYLOYL GLYCERIN/SEBACIC ACID COPOLYMER (2000 MPA.S); DISTEARDIMONIUM HECTORITE; TRIHYDROXYSTEARIN; APPLE; DIHEPTYL SUCCINATE; HYDROXYACETOPHENONE; FERRIC OXIDE RED; SODIUM DEHYDROACETATE; TOCOPHEROL; POLYMETHYLSILSESQUIOXANE (4.5 MICRONS); SQUALANE; PHENOXYETHANOL; MEDIUM-CHAIN TRIGLYCERIDES; FERRIC OXIDE YELLOW; BUTYLOCTYL SALICYLATE; GLYCERIN; JOJOBA OIL, RANDOMIZED; GLYCYRRHIZINATE DIPOTASSIUM; FERROSOFERRIC OXIDE; SODIUM CHLORIDE; POLYHYDROXYSTEARIC ACID (2300 MW); TRIETHYL CITRATE; AVOCADO OIL; SODIUM CITRATE; BEET; WATER; C9-12 ALKANE; DIMETHICONE; ETHYLHEXYL OLIVATE

Wonderscreen Tinted Broad Spectrum SPF 30 Shade 3

Acitve ingredient:

Zinc Oxide 19.0%

Purpose: Sunscreen

Uses:

- Helps prevent sunburn

Keep out of reach of children. If product is swallowed, get medical help or contact a Poison Control Center right away.

Stop use and ask a doctor if rash occurs.

Warning:

- For External use only Do not use on broken or damaged skin. when using this product keep out of eyes. Rinse with water to remove

Directions:

- Apply liberally 15 minutes before sun or water exposure
- Immediately after towel drying
- At least every 2 hours
- Children under 6 month: Ask a doctor

INACTIVE INGREDIENT

Inactive Ingredients: Water, Ethylhexyl Olivate, Dimethicone, C9-12 Alkane, Cocoglycerides, Caprylic/Capric Triglyceride, Hydroxyethyl Dimethicone Laurate, Pentylene Glycol, Iron Oxides (CI 77492), Butyloctyl Salicylate, Glycerin, Jojoba Esters, Pyrus Malus (Apple) Fruit Extract, Polymethylsilsesquioxane, Diheptyl Succinate, Disteardimonium Hectorite, Squalane, Phenoxyethanol, Sodium Chloride, Iron Oxides (CI 77499), Polyhydroxystearic Acid, Trihydroxystearin, Iron Oxides (CI 77491), Triethyl Citrate, Hydroxyacetophenone, Persea Gratissima (Avocado) Oil, Dipotassium Glycyrrhizate, Fructooligosaccharides, Sodium Citrate, Beta Vulgaris (Beet) Root Extract, Hydrogenated Vegetable Oil, Tetrasodium Glutamate Diacetate, Sodium Dehydroacetate, Capryloyl Glycerin/Sebacic acid Copolymer, Glycine Soja (Soybean) Seed Extract, Tocopherol

PACKAGE LABEL

Dime
Wonderscreen
Tinted Broad Spectrum SPF 30
50 G